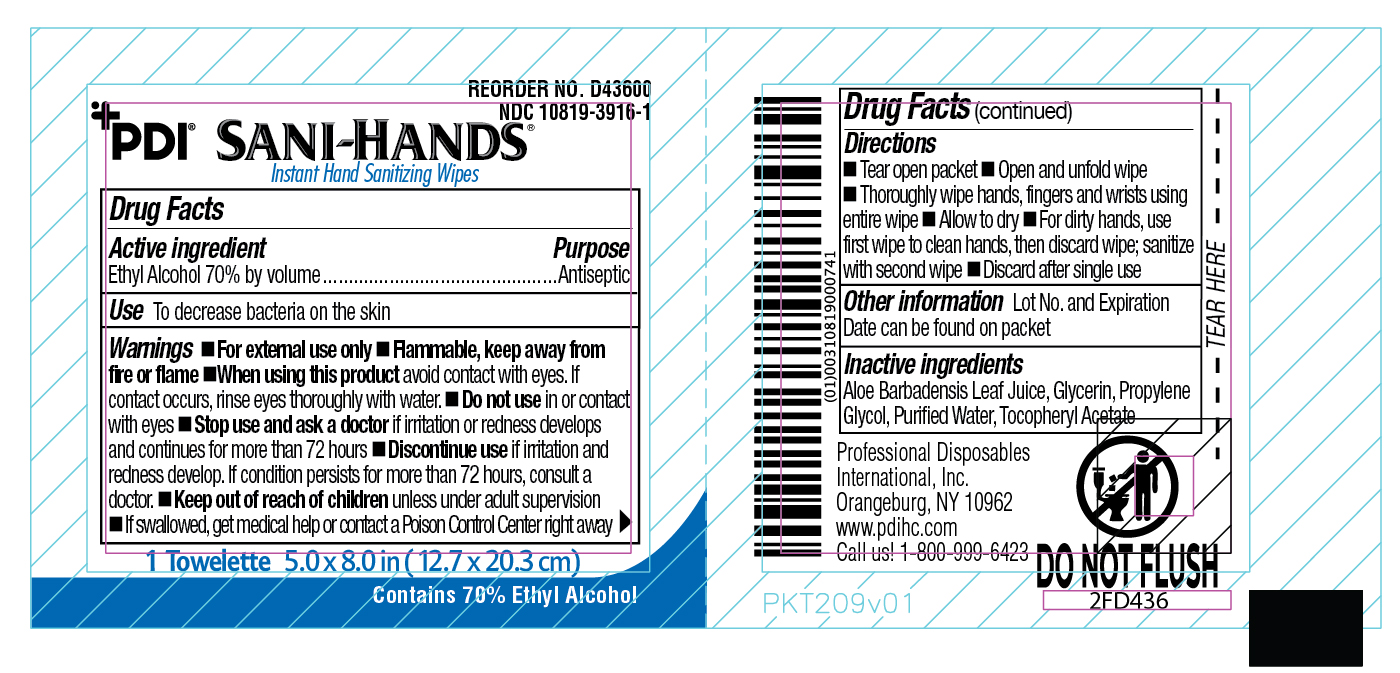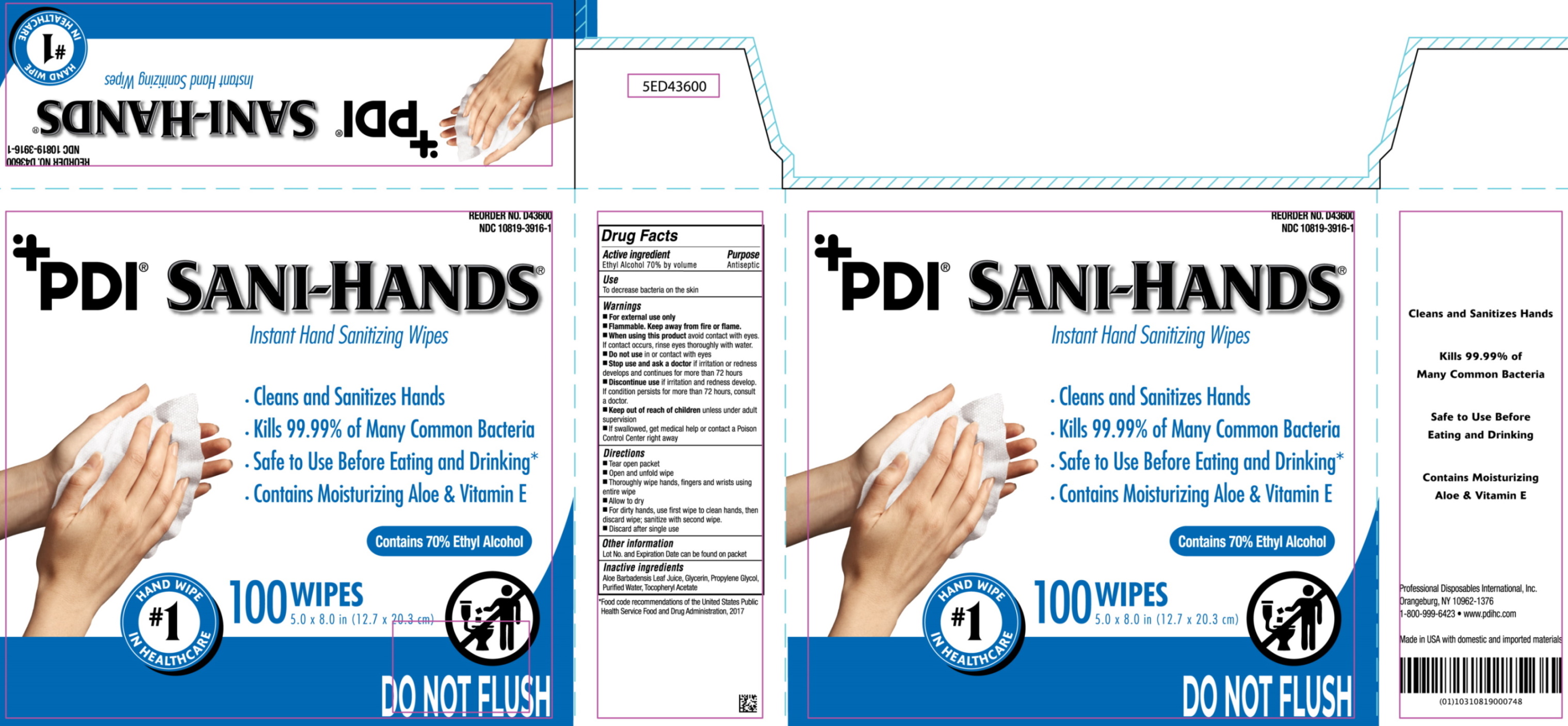 DRUG LABEL: PDI Sani-Hands
NDC: 10819-3916 | Form: CLOTH
Manufacturer: Professional Disposables International, Inc.
Category: otc | Type: HUMAN OTC DRUG LABEL
Date: 20240821

ACTIVE INGREDIENTS: ALCOHOL 0.7 mL/1 mL
INACTIVE INGREDIENTS: WATER; PROPYLENE GLYCOL; GLYCERIN; ALOE VERA LEAF; ALPHA-TOCOPHEROL ACETATE

PDI Sani Hands

Uses

To decrease bacteria on the skin

Warnings

- For external use only
- Flammable, keep away from fire or flame
- When using this product avoid contact with eyes. If contact occurs, rinse eyes thoroughly with water
- Do not use in or contact with eyes.
- Stop use and ask a doctor if irritation and redness develop. If condition persists for more than 72 hours, consult a doctor.

Inactive ingredients

Aloe Barbadensis Leaf Juice, Glycerin, Propylene Glycol, Purified Water, Tocopheryl Acetate

Active ingredient

Ethyl Alcohol 70% by volume

Purpose

Antiseptic

Directions

- Tear open packet
- Open and unfold wipe
- Thoroughly wipe hands, fingers and wrists using entire
- Allow to dry
- For dirty hands, use first wipe to clean hands, then discard wipe. Sanitize with second wipe.
- Discard after single use

Keep out of reach of children unless under adult supervision.

If swallowed, get medical help or contact a Poison Control Center immediately.

Other information

Lot No. and Expiration Date can be found on packet.

PACKAGE LABEL

packet

box